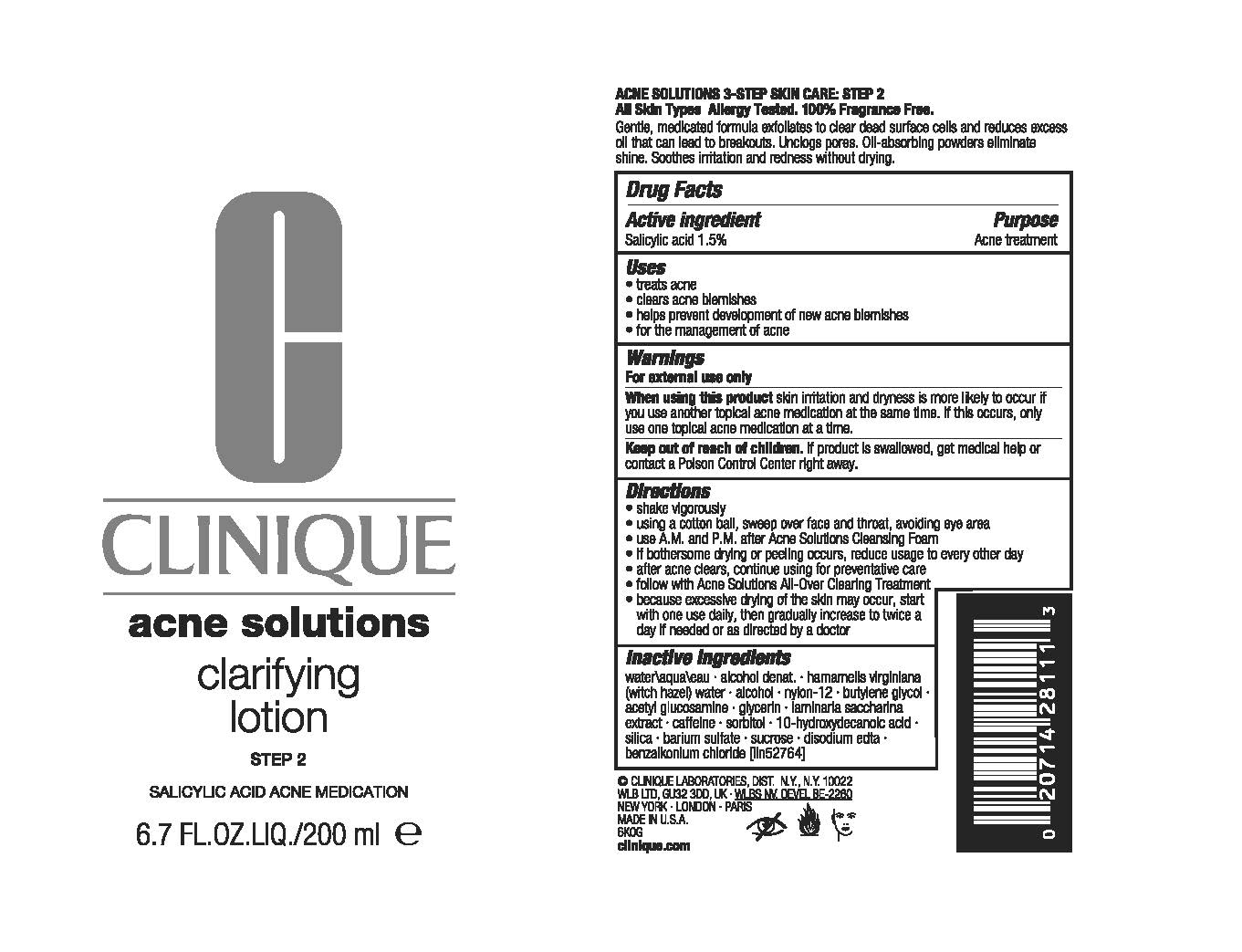 DRUG LABEL: ACNE solutions CLARIFYING
NDC: 49527-723 | Form: LIQUID
Manufacturer: CLINIQUE LABORATORIES LLC
Category: otc | Type: HUMAN OTC DRUG LABEL
Date: 20241118

ACTIVE INGREDIENTS: SALICYLIC ACID 15 mg/1 mL
INACTIVE INGREDIENTS: WATER; NYLON-12; BUTYLENE GLYCOL; HAMAMELIS VIRGINIANA ROOT BARK/STEM BARK; SACCHARINA LATISSIMA; CAFFEINE; SUCROSE; GLYCERIN; N-ACETYLGLUCOSAMINE; SORBITOL; PSEUDOPTEROGORGIA ELISABETHAE; BARIUM SULFATE; 10-HYDROXYDECANOIC ACID; SILICON DIOXIDE; EDETATE DISODIUM; BENZALKONIUM CHLORIDE

ACNE SOLUTIONS CLARIFYING LOTION

Active ingredient

Salicylic acid 1.5%

Purpose

Acne treatment

Uses

- treats acne
- clears acne blemishes
- helps prevent development of new acne blemishes
- for the management of acne

Warnings

For external use only.

When using this product skin irritation and dryness is more likely to occur if you use another topical acne medication at the same time. If this occurs, only use one topical acne medication at a time.

Keep out of reach of children. If swallowed, get medical help or contact a Poison Control Center right away.

Directions

- shake vigorously
- using a cotton ball, sweep over face and throat, avoiding eye area
- use AM and PM after Acne Solutions Cleansing Foam
- if bothersome drying or peeling occurs, reduce usage to every other day
- after acne clears, continue using for preventative care
- follow with Acne Solutions All-Over Clearing Treatment
- because excessive drying of the skin may occur, start with one use daily, then gradually increase to twice a day if needed or as directed by a doctor

Inactive ingredients

water\aqua\eau,alcohol denat.,hamamelis virginiana (witch hazel) water,alcohol,nylon-12,butylene glycol,acetyl glucosamine,glycerin,laminaria saccharina extract,caffeine,sorbitol,10-hydroxydecanoic acid,silica,barium sulfate,sucrose,disodium edta,benzalkonium chloride <iln52764>

PRINCIPAL DISPLAY PANEL - 200 ml Bottle

CLINIQUE

acne solutions

clarifying lotion

STEP 2
SALICYLIC ACID ACNE MEDICATION

6.7 FL.OZ./200 ml e